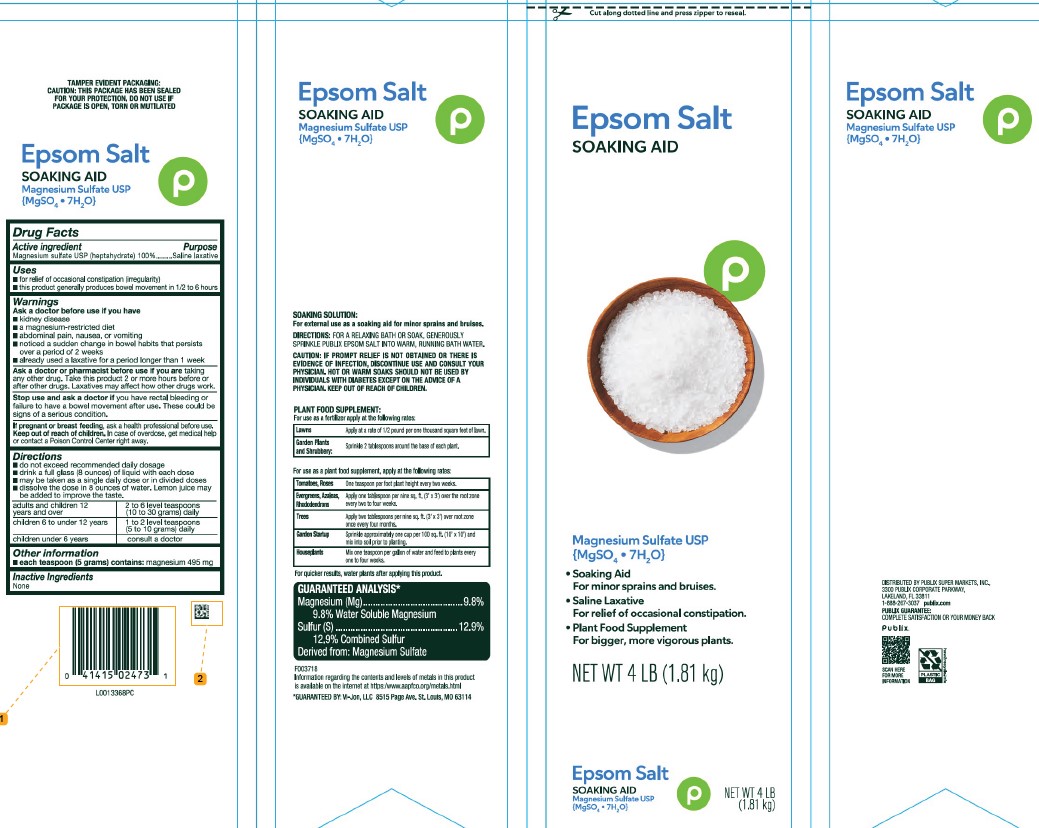 DRUG LABEL: Epsom Salt
NDC: 56062-952 | Form: GRANULE
Manufacturer: Publix Super Markets, Inc.
Category: otc | Type: HUMAN OTC DRUG LABEL
Date: 20260205

ACTIVE INGREDIENTS: MAGNESIUM SULFATE HEPTAHYDRATE 1 g/1 g

Publix 029.003/029AA
Epsom Salt 3 in 1

Tamper Evident Statement

TAMPER EVIDENT PACKAGING:

CAUTION: THIS PACKAGE HAS BEEN SEALED FOR YOUR PROTECTION. DO NOT USE IF PACKAGE IS OPEN, TORN, OR MUTILATED

Claim

Epsom Salt

SOAKING AID

MAGNESIUM SULFATE U.S.P.

{MgSO4• 7H2O}

P

Active ingredient

Magnesium sulfate USP (heptahydrate) 100%

Purpose

Saline Laxative

Uses

- for relief of occasional constipation (irregularity)
- this product generally produces bowel movement in 1/2 to 6 hours

Warnings

for this product

Ask a doctor before use if you have

- kidney disease
- a magnesium-restricted diet
- abdominal pain, nausea, or vomiting
- noticed a sudden change in bowel habits that persists over a period of 2 weeks
- already used a laxative for a period longer than 1 week

Ask a doctor or pharmacist before use if you are

taking any other drug. Take this product 2 or more hours before or after other drugs. Laxatives may affect how other drugs work.

Stop use and ask a doctor if

you have rectal bleeding or failure to have a bowel movement after use. These could be signs of a serious condition.

If pregnant or breast-feeding,

ask a health professional before use.

Keep out of rech of children.

In case of overdose, get medical help or contact a Poison Control Center right away.

Directions

- do not exceed recommended daily dosage
- drink a full glass (8 ounces) of liquid with each dose
- may be taken as a single daily dose or in divided doses
- dissolve the dose in 8 ounces of water. Lemon juice may be added to improve the taste.

adults and children 12 years and over - 2 to 6 level teaspoons (10 to 30 grams) daily

children 6 to under 12 years - 1 to 2 level teaspoons (5 to 10 grams) daily

children under 6 years - consult a doctor

Inactive Ingredients

None

Other information

- each teaspoon (5 grams) contains: magnesium 495 mg

ADVERSE REACTION

DISTRIBUTED BY PUBLIX SUPER MARKETS, INC.,

3300 PUBLIX CORPORATE PARKWAY,

LAKELAND, FL 33802

1-888-267-3037 publix.com

PUBLIX GUARANTEE:

COMPLETE SATISFACTION OR YOUR MONEY BACK

Publix

SCAN HERE FOR MORE INFORMATION

PLASTIC BAG

how2recycle.info

Side panel claims

Epsom Salt

SOAKING AID

MAGNESIUM SULFATE U.S.P.

{MgSO4• 7H2O}

P

SOAKING SOLUTION:

FOR EXTERNAL USE AS A SOAKING AID FOR MINOT SPRAINS AND BRUISES.

DIRECTIONS:FOR A RELAXING BATH OR SOAK, GENEROUSLY SPRINKLE PUBLIX EPSOM SALT INTO WARM, RUNNING BATH WATER.

CAUTION: IF PROMPT RELIEF IS NOT OBTAINED OR THERE IS EVIDENCE OF INFECTION, DISCONTINUE USE AND CONSULT YOUR PHYSICIAN. HOT OR WARM SOAKS SHOULD NOT BE USED BY INDIVIDUALS WITH DIABETES EXCEPT ON THE ADIVCE OF A PHYSICIAN.

KEEP OUT OF REACH OF CHILDREN.

Plant Food Supplement:
For use as a fertilizer, apply at the following rates:

LAWNSApply at a rate of ½ pound per one thousand square feet of lawn.

Garden Plants and ShrubberySprinkle 2 tablespoons around the base of each plant.

For use as a Plant Food Supplement, apply at the following rates:

Tomatoes, RosesOne teaspoon per foot plant height every two weeks.

Evergreens, Rhododendrons, AzaleasApply one tablespoon per nine sq. ft. (3’ X 3’) over the root zone every two to four weeks.

TreesApply two tablespoons per nine sq. ft. (3’ X 3’) over root zone once every four months.

Garden StartupSprinkle approximately one cup per 100 sq. ft. (10’ X 10’) and mix into soil prior to planting.

HouseplantsMix one teaspoon per gallon of water and feed to plants every one to four weeks.

For quicker results, water plants after applying this product.

GUARANTEED ANALYSIS*

Magnesium (Mg) ..........................9.8%
9.8% Water Soluble Magnesium
Sulfur (S) .............................12.9%
12.9% Combined Sulfur

Derived from: Mgnesium Sulfate

F003718

Information regarding the contents and levels of metals in this product is available on the internet at:

https:/www.aapfco.org/metals.html

*GUARANTEED BY: Vi-Jon, LLC
8515 Page Ave.
St. Louis, MO 63114

principal display panel

Cut along dotted line and press zipper to reseal.

Epsom Salt

SOAKING AID

P

MAGNESIUM SULFATE U.S.P.

{MgSO4 • 7H2O}

- Soaking Aid

For minor sprains and bruises

- Saline Laxative

For relief of occasional constipation

- Plant Food Supplement

For bigger, more vigorous plants

NET WT 4 LB (1.81 kg)

Epsom Salt

SOAKING AID

MAGNESIUM SULFATE U.S.P.

{MgSO4• 7H2O}

P

NET WT 4 LB (1.81 kg)